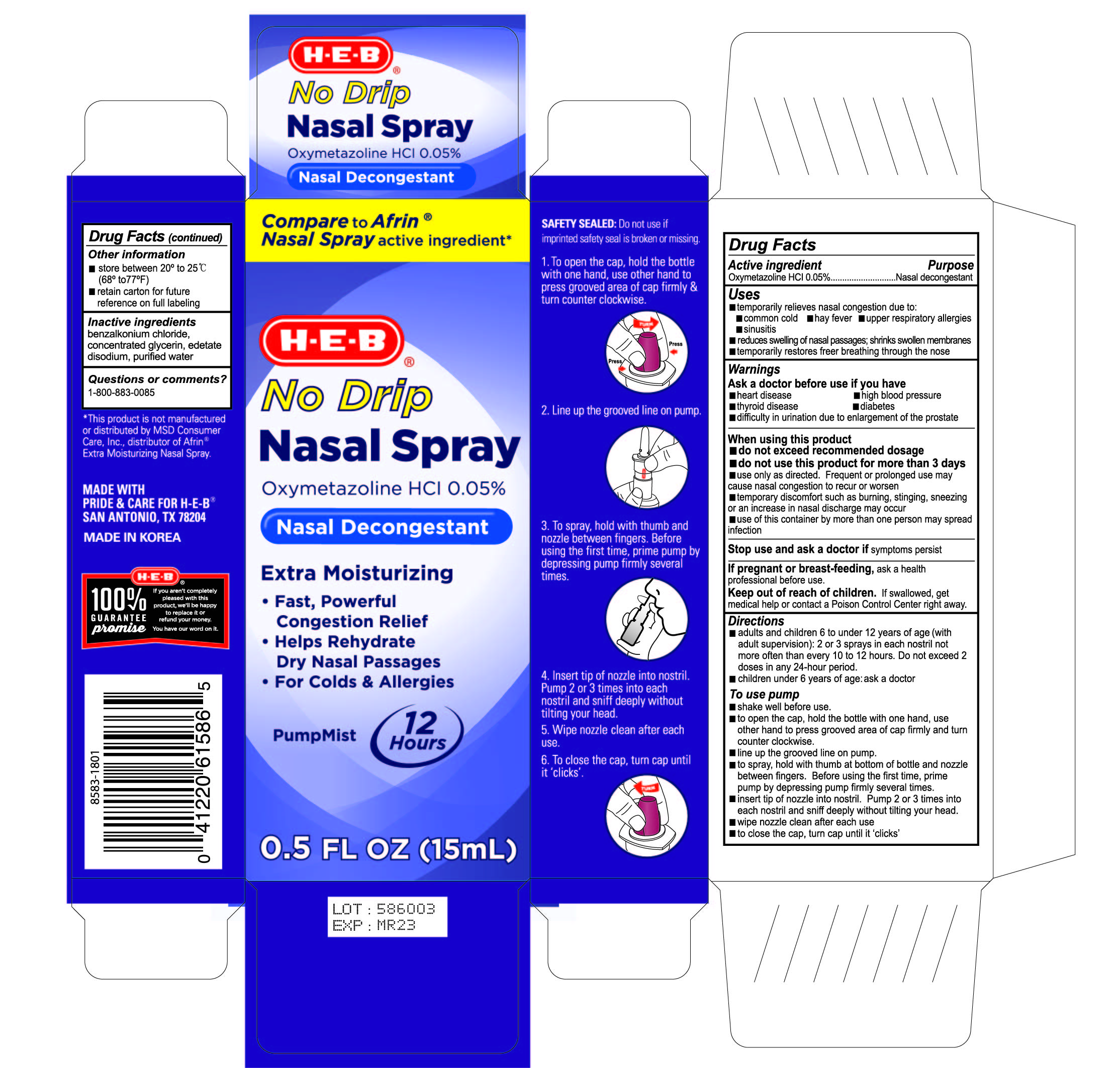 DRUG LABEL: HEB Nasal decongestant No Drip Extra Moisturizing
NDC: 37808-412 | Form: SOLUTION
Manufacturer: H-E-B
Category: otc | Type: HUMAN OTC DRUG LABEL
Date: 20200406

ACTIVE INGREDIENTS: OXYMETAZOLINE HYDROCHLORIDE 0.05 g/100 mL
INACTIVE INGREDIENTS: GLYCERIN; WATER; BENZALKONIUM CHLORIDE; EDETATE DISODIUM

HEB Nasal Spray

Drug Facts

Active ingredient

Oxymetazoline hydrochloride 0.05%

Purpose

Nasal decongestant

Uses

- temporarily relieves nasal congestion due to:
- common cold
- hay fever
- upper respiratory allergies
- sinusitis
- reduces swelling of nasal passages; shrinks swollen membranes
- temporarily restores freer breathing through the nose

Warnings

Ask a doctor before use if you have

- heart disease
- high blood pressure
- thyroid disease
- diabetes
- trouble urinating due to an enlarged prostate gland

When using this product

- do not exceed recommended dosage
- do not use for more than 3 days.
- use only as directed. Frequent or prolonged use may cause nasal congestion to recur or worsen.
- temporary discomfort such as burning, stinging, sneezing, or an increase in nasal discharge may occur
- use of this container by more than one person may spread infection

Stop use and ask a doctor if symptoms persist

PREGNANCY OR BREAST FEEDING

If pregnant or breast-feeding, ask a health professional before use.

Keep out of reach of children. If swallowed, get medical help or contact a Poison Control Center right away.

Directions

- adults and children 6 to under 12 years of age (with adult supervision): 2 or 3 sprays in each nostril not more often than every 10 to 12 hours. Do not exceed 2 doses in any 24-hour period.
- children under 6 years of age: ask a doctor

To use Pump

- shake well before use
- to open the cap, hold the bottle with one hand, use the other hand to press groved area of cap firmly and turn counter closwise
- line up the grooved line on the pump
- to spray, hold with thumb at bottom of the bottle andnozzle between fingers. Before using the first time, prime pump by depressing pump firmly several times.
- insert tip of nozzle into nostril. Pump 2 or 3 times into each nostril and sniff deeply without tilting head.
- wipe nozzle clean after each use
- to close the cap, turn unitl it 'clicks'

Other information

- store between 20-25°C (68-77°F)
- retain carton for future reference on full labelling

Inactive ingredients

benzalkonium chloride, concentrated glycerin, edetate disodium, purified water,

Questions or comments?

1-800-883-0085